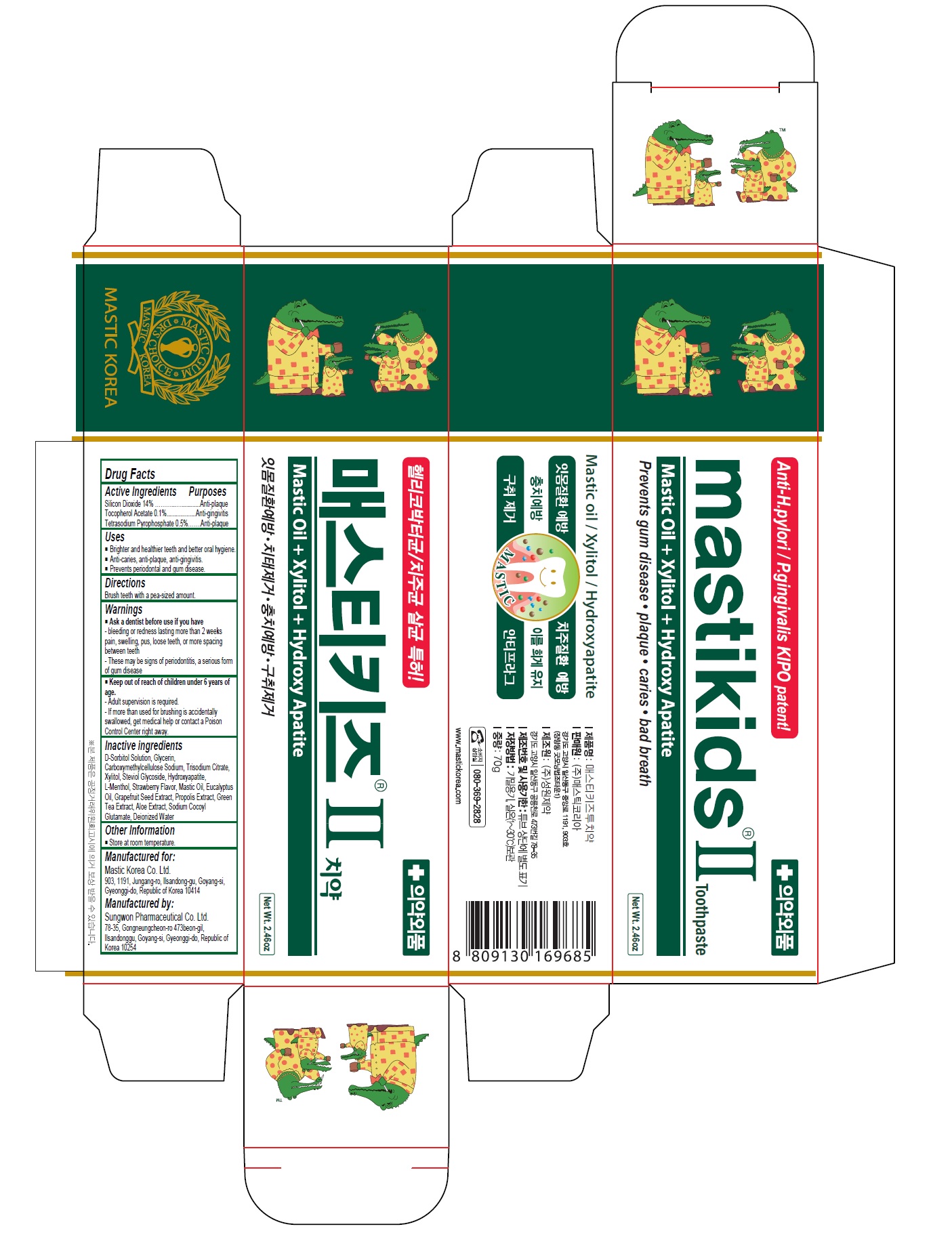 DRUG LABEL: Mastikids II
NDC: 79814-005 | Form: PASTE, DENTIFRICE
Manufacturer: Mastic Korea.Co.Ltd
Category: otc | Type: HUMAN OTC DRUG LABEL
Date: 20200914

ACTIVE INGREDIENTS: SILICON DIOXIDE 14 g/100 g; .ALPHA.-TOCOPHEROL ACETATE 0.1 g/100 g; SODIUM PYROPHOSPHATE 0.5 g/100 g
INACTIVE INGREDIENTS: SORBITOL; GLYCERIN; CARBOXYMETHYLCELLULOSE SODIUM, UNSPECIFIED; SODIUM CITRATE, UNSPECIFIED FORM; XYLITOL; STEVIOSIDE; TRIBASIC CALCIUM PHOSPHATE; LEVOMENTHOL; STRAWBERRY; EUCALYPTUS OIL; CITRUS PARADISI SEED; PROPOLIS WAX; GREEN TEA LEAF; ALOE; SODIUM COCOYL GLUTAMATE; WATER

79814-005_Mastikids II toothpaste

ACTIVE INGREDIENT

Silicon Dioxide 14%

Tocopherel Acetate 0.1%

Tetrasodium Pyrophosphate 0.5%

INACTIVE INGREDIENT

D-Sorbitol Solution, Glycerin, Carboxymethylcellulose Sodium, Trisodium Citrate, Xylitol, Steviol Glycoside, Hydroxyapatite, L-Menthol, Strawberry Flavor, Mastic Oil, Eucalyptus Oil, Grapefruit Seed Extract, Propolis Extract, Green Tea Extract, Aloe Extract, Sodium Cocoyl Glutamate, Deionized Water

Keep out of Reach of Children.

PURPOSE

Anti-gingivitis

Anti-plaque

WARNINGS

Ask a dentist before use if you have

- bleeding or redness lasting more than 2 weeks pain, swelling, pus, losse teeth, or more spacing between teeth

- These may be signs of periodontitis, a serious form of gum disease

INDICATIONS AND USAGE

- Brighter and healthier teeth and better oral hygiene

- Anti-caries, anti-plaque, anti--gingivitis

- Prevents periodontal and gum disease

DOSAGE AND ADMINISTRATION

Brush teeth with a pea-sized amount